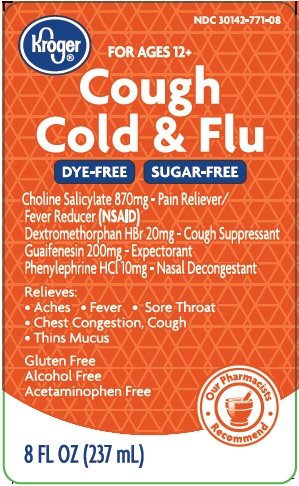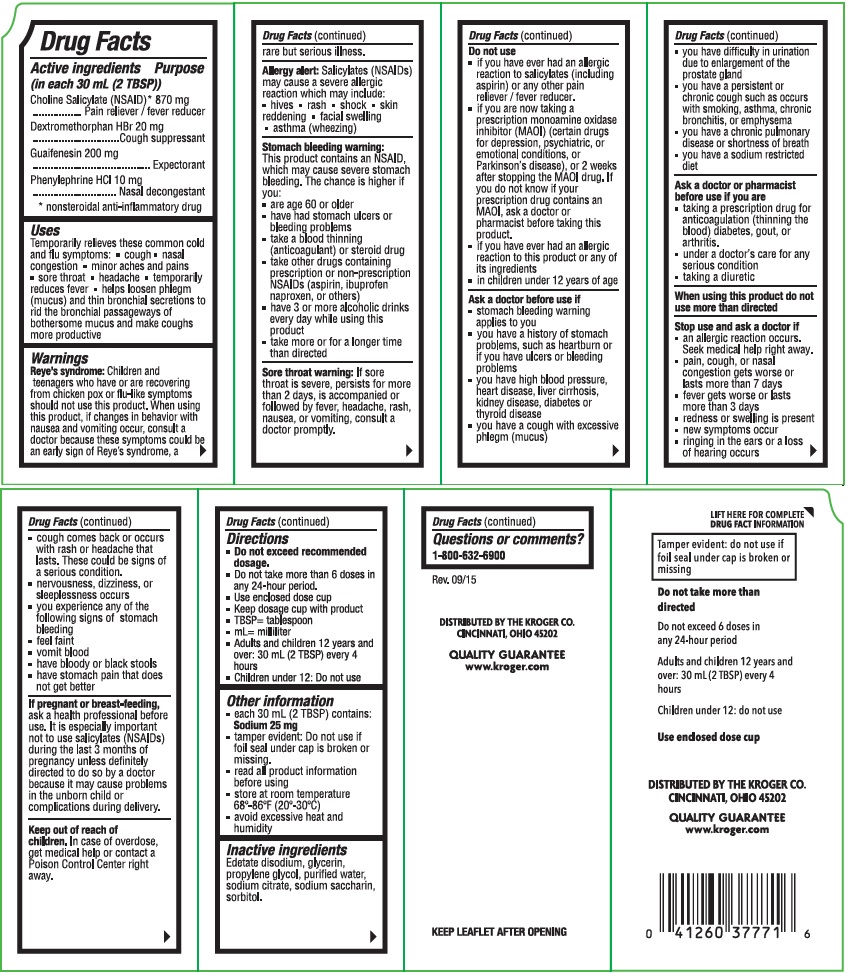 DRUG LABEL: Kroger Cough Cold and Flu
NDC: 30142-771 | Form: LIQUID
Manufacturer: THE KROGER CO
Category: otc | Type: HUMAN OTC DRUG LABEL
Date: 20160630

ACTIVE INGREDIENTS: CHOLINE SALICYLATE 870 mg/30 mL; PHENYLEPHRINE HYDROCHLORIDE 10 mg/30 mL; DEXTROMETHORPHAN HYDROBROMIDE 20 mg/30 mL; GUAIFENESIN 200 mg/30 mL
INACTIVE INGREDIENTS: EDETATE DISODIUM; PROPYLENE GLYCOL; SODIUM CITRATE; SACCHARIN SODIUM; SORBITOL; WATER; GLYCERIN

Kroger Cough Cold & Flu

Drug Facts

Active ingredients

(in each 30 mL (2TBSP))

Choline Salicylate (NSAID)* 870 mg

Dextromethorphan HBr 20 mg

Guaifenesin 200 mg

Phenylephrine HCl 10 mg

*nonsteroidal anti-inflammatory drug

Purpose

Pain reliever / fever reducer

Cough suppressant

Expectorant

Nasal decongestant

Uses

Temporarily relieves these common cold and flu symptoms:

- cough
- nasal congestion
- minor aches and pains
- sore throat
- headache
- temporarily reduces fever
- helps loosen phlegm (mucus) and thin bronchial secretions to rid the bronchial passageways of bothersome mucus and make coughs more productive

Warnings

Reye's syndrome: Children and teenagers who have or are recovering from chicken pox or flu-like symptoms should not use this product. If changes in behavior with nausea and vomiting occur, consult a doctor because these symptoms could be an early sign of Reye's syndrome, a rare but serious illness.

Allergy alert: Salicylates (NSAIDs) may cause a severe allergic reaction which may include:

- hives
- rash
- shock
- skin reddening
- facial swelling
- asthma (wheezing)

Stomach bleeding warning:

This product contains an NSAID, which may cause severe stomach bleeding. The chance is higher if you:

- are age 60 or older
- have had stomach ulcers or bleeding problems
- take a blood thinning (anticoagulant) or steroid drug
- take other drugs containing prescription or non-prescription NSAIDs (aspirin, ibuprofen, naproxen, or others)
- have 3 or more alcoholic drinks every day while using this product
- take more or for a longer time than directed

Sore throat warning: If sore throat is severe, persists for more than 2 days, is accompanied or followed by fever, headache, rash, nausea, or vomiting, consult a doctor promptly.

Do not use

- if you have had an allergic reaction to salicylates (including aspirin) or any other pain reliever / fever reducer.
- if you are now taking a prescription monoamine oxidase inhibitor (MAOI) (certain drugs for depression, psychiatric, or emotional conditions, or Parkinson's disease), or 2 weeks after stopping the MAOI durg. If you do not know if your prescription drug contains an MAOI, ask a doctor or pharmacist before taking this product.
- if you have ever had an allergic reaction to this product or any of its ingredients
- in children under 12 years of age

Ask a doctor before use if

- stomach bleeding warning applies to you
- you have a history of stomach problems, such as heartburn or if you have ulcers or bleeding problems
- you have high blood pressure, heart disease, liver cirrhosis, kidney disease, diabetes, or thyroid disease
- you have a cough with excessive phlegm (mucus)
- you have difficulty in urination due to enlargement of the prostate gland
- you have a persistent or chronic cough such as occurs with smoking, asthma, chronic bronchitis, or emphysema
- you have a chronic pulmonary disease or shortness of breath
- you have a sodium restricted diet

Ask a doctor or pharmacist before use if you are

- taking a prescription drug for anticoagulation (thinning the blood) diabetes, gout, or arthritis.
- under a doctor's care for any serious condition
- taking a diuretic

When using this product do not use more than directed

Stop use and ask a doctor if

- an allergic reaction occurs. Seek medical help right away.
- pain, cough, or nasal congestion gets worse or lasts more than 7 days
- fever gets worse or lasts more than 3 days
- redness or swelling is present
- new symptoms occur
- ringing in the ears or a loss of hearling occurs
- cough comes back or occurs with rash or headache that lasts. These could be signs of a serious condition.
- nervousness, dizziness, or sleeplessness occurs
- you experience any of the following signs of stomach bleeding
- feel faint
- vomit blood
- have bloody or black stools
- have stomach pain that does not get better

PREGNANCY OR BREAST FEEDING

If pregnant or breast-feeding, ask a health professional before use. It is especially important not to use salicylates (NSAIDs) during the last 3 months of pregnancy unless definitely directed to do so by a doctor because it may cause problems in the unborn child or complications during delivery.

Keep out of reach of children. In case of overdose, get medical help or contact a Poison Control Center right away.

Directions

- Do not exceed recommended dosage.
- Do not take more than 6 doses in any 24-hour period.
- Use enclosed dose cup
- Keep dosage cup with product
- TBSP=tablespoon
- mL=milliliter
- Adults and children 12 years and over: 30 mL (2 TBSP) every 4 hours
- Children under 12: Do not use

Other information

- each 30 mL (2 TBSP) contains: Sodium 25 mg
- tamper evident: Do not use if foil seal under cap is broken or missing.
- read all product information before using
- store at room temperature 68°-86°F (20°-30°C)
- avoid excessive heat and humidity

Inactive ingredients

Edetate sodium, glycerin, propylene glycol, purified water, sodium citrate, sodium saccharin, sorbitol.

Questions or comments?

1-800-632-6900